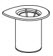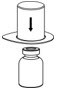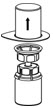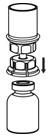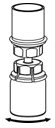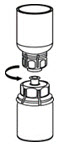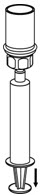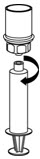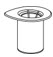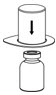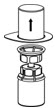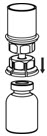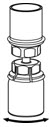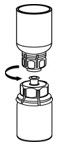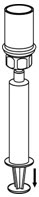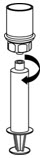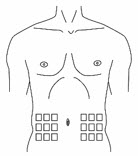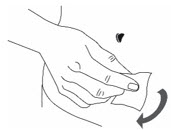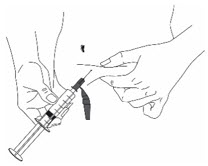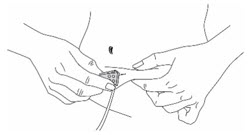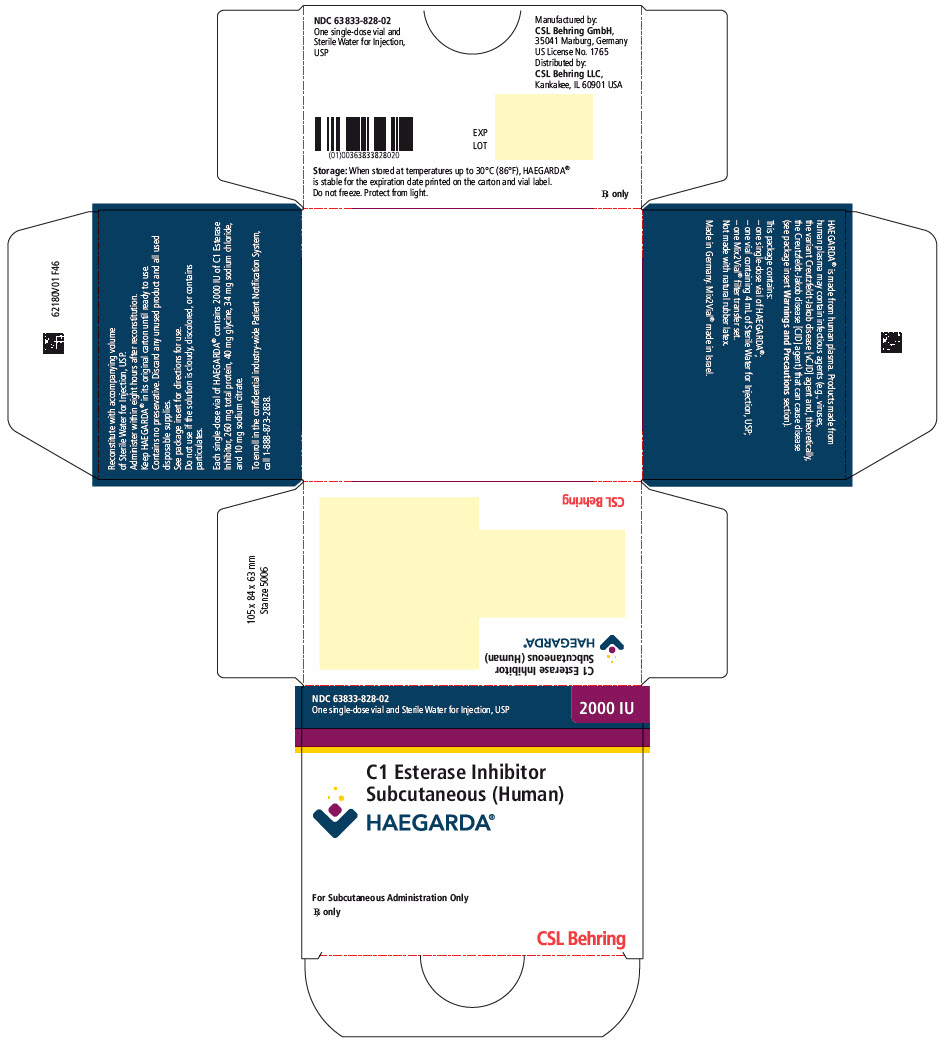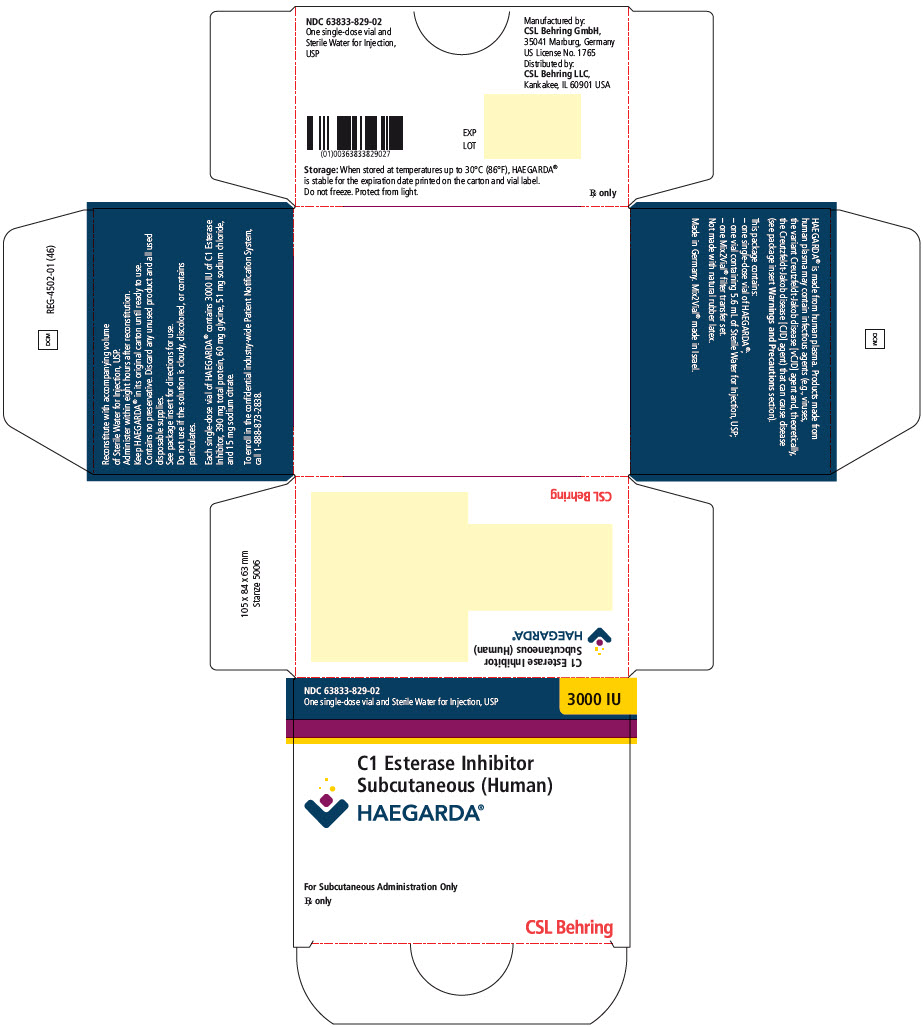 DRUG LABEL: HAEGARDA
NDC: 63833-828 | Form: KIT | Route: SUBCUTANEOUS
Manufacturer: CSL Behring GmbH
Category: other | Type: PLASMA DERIVATIVE
Date: 20220204

ACTIVE INGREDIENTS: HUMAN C1-ESTERASE INHIBITOR 2000 [iU]/4 mL
INACTIVE INGREDIENTS: Glycine 40 mg/4 mL; Sodium Chloride 34 mg/4 mL; Sodium Citrate, Unspecified Form 10 mg/4 mL; Water

HIGHLIGHTS OF PRESCRIBING INFORMATION

These highlights do not include all the information needed to use HAEGARDA safely and effectively. See full prescribing information for HAEGARDA.
HAEGARDA® (C1 Esterase Inhibitor Subcutaneous [Human])
For Subcutaneous Injection, Freeze-Dried Powder for Reconstitution
Initial U.S. Approval: 2017

RECENT MAJOR CHANGES

Indications and Usage (1) | 09/2020

1 INDICATIONS AND USAGE

HAEGARDA is a plasma-derived concentrate of C1 Esterase Inhibitor (Human) (C1-INH) indicated for routine prophylaxis to prevent Hereditary Angioedema (HAE) attacks in patients 6 years of age and older. (1)

2 DOSAGE AND ADMINISTRATION

For subcutaneous use after reconstitution only.

- Administer 60 International Units per kg body weight twice weekly (every 3 or 4 days). (2)
- Reconstitute HAEGARDA prior to use using Sterile Water for Injection, USP. (2.1)
- Use a silicone-free syringe for reconstitution and administration. (2.1)
- Administer at room temperature within 8 hours after reconstitution. (2.1)

3 DOSAGE FORMS AND STRENGTHS

HAEGARDA is available as a white lyophilized powder supplied in single-dose vials containing 2000 or 3000 International Units (IU) of C1-INH. (3)

4 CONTRAINDICATIONS

Do not use in patients with a history of life-threatening immediate hypersensitivity reactions, including anaphylaxis to C1-INH preparations or its excipients. (4)

5 WARNINGS AND PRECAUTIONS

- Severe hypersensitivity reactions may occur. In case of severe hypersensitivity, discontinue HAEGARDA administration and institute appropriate treatment. Epinephrine should be immediately available for treatment of severe hypersensitivity reaction. (5.1)
- At the recommended subcutaneous (S.C.) dose, a causal relationship between thromboembolic events (TEEs) and the use of HAEGARDA has not been established. However, thrombosis has occurred in treatment attempts with high doses of C1-INH intravenous (I.V.) for prevention or therapy of capillary leak syndrome before, during or after cardiac surgery (unapproved indication and dose). (5.2)
- Because HAEGARDA is made from human blood, it may carry a risk of transmitting infectious agents, e.g., viruses, the variant Creutzfeldt-Jakob disease (vCJD) agent and, theoretically, the Creutzfeldt-Jakob disease (CJD) agent. (5.3)

6 ADVERSE REACTIONS

- Adverse reactions occurring in more than 4% of subjects treated with HAEGARDA were injection site reactions, hypersensitivity, nasopharyngitis and dizziness. (6.1)

To report SUSPECTED ADVERSE REACTIONS, contact the CSL Behring Pharmacovigilance Department at 1-866-915-6958 or FDA at 1-800-FDA-1088 or www.fda.gov/medwatch.

FULL PRESCRIBING INFORMATION

1 INDICATIONS AND USAGE

HAEGARDA is a plasma-derived concentrate of C1 Esterase Inhibitor (Human) (C1-INH) indicated for routine prophylaxis to prevent Hereditary Angioedema (HAE) attacks in patients 6 years of age and older.

2 DOSAGE AND ADMINISTRATION

After reconstitution, for subcutaneous use only.

HAEGARDA is intended for self (or caregiver)-administration after reconstitution at a dose of 60 International Units (IU) per kg body weight by subcutaneous (S.C.) injection twice weekly (every 3 or 4 days). The patient or caregiver should be trained on how to administer HAEGARDA.

HAEGARDA is provided as a freeze-dried powder for reconstitution with Sterile Water for Injection, USP.

2.1 Preparation and Handling

- Check the expiration date on the product vial label. Do not use beyond the expiration date.
- Work on a clean surface and wash hands before performing the following procedures.
- Prepare and administer using aseptic techniques [see Dosage and Administration (2.2)].
- Use a silicone-free syringe for reconstitution and administration.
- Each vial of HAEGARDA is for single-dose only. Promptly use the reconstituted solution. The solution must be used within 8 hours. Discard partially used vials. HAEGARDA contains no preservative.
- Do not freeze the reconstituted solution.

2.2 Reconstitution and Administration

Use either the Mix2Vial® transfer set provided with HAEGARDA or a commercially available double-ended needle and vented filter spike [see How Supplied/Storage and Handling (16)].

Reconstitution

The procedures below are provided as general guidelines for the reconstitution and administration of HAEGARDA.

HAEGARDA Reconstitution Instructions

1. Ensure that the HAEGARDA vial and Sterile Water for Injection (diluent) vial are at room temperature.

2. Place the HAEGARDA vial, diluent vial and Mix2Vial transfer set on a flat surface.

3. Remove flip caps from the HAEGARDA and diluent vials.

4. Wipe the stoppers with an alcohol swab and allow to dry prior to opening the Mix2Vial transfer set package.

5. Open the Mix2Vial transfer set package by peeling away the lid (Figure 1). Do not remove the device from the package.

Figure 1

6. Place the diluent vial on a flat surface and hold the vial tightly. Grip the Mix2Vial transfer set together with the clear package and push the plastic spike at the blue end of the Mix2Vial transfer set firmly through the center of the stopper of the diluent vial (Figure 2).

Figure 2

7. Carefully remove the clear package from the Mix2Vial transfer set. Do not remove the Mix2Vial transfer set or touch the exposed end of the device (Figure 3).

Figure 3

8. With the HAEGARDA vial placed firmly on a flat surface, invert the diluent vial with the Mix2Vial transfer set attached and push the plastic spike of the transparent adapter firmly through the center of the stopper of the HAEGARDA vial (Figure 4). The diluent will automatically transfer into the HAEGARDA vial.

Figure 4

9. With the diluent and HAEGARDA vial still attached to the Mix2Vial transfer set, gently swirl the HAEGARDA vial to ensure that the powder is fully dissolved (Figure 5). Do not shake the vial.

Figure 5

10. With one hand, grasp the HAEGARDA side of the Mix2Vial transfer set and with the other hand grasp the blue diluent side of the Mix2Vial transfer set, and unscrew the set into two pieces (Figure 6).

Figure 6

11. Draw air into an empty, sterile syringe. Use a silicone-free syringe. While the HAEGARDA vial is upright, screw the syringe to the Mix2Vial transfer set. Inject air into the HAEGARDA vial.

12. While keeping the syringe plunger pressed, invert the system upside down and draw the concentrate into the syringe by pulling the plunger back slowly (Figure 7).

Figure 7

13. Disconnect the filled syringe by unscrewing it from the Mix2Vial transfer set (Figure 8). The reconstituted solution should be colorless, clear, and free from visible particles. Do not use if particles or discoloration are observed.

Figure 8

14. Use immediately or within 8 hours of reconstitution. Store reconstituted solution at room temperature. Do not refrigerate.

15. If the dose requires more than one vial, use a separate, unused Mix2Vial transfer set and diluent vial for each product vial. Repeat steps 10-12 to pool the contents of the vials into one syringe.

Administration

For subcutaneous injection only.

- Train the patient or caregiver on how to self-administer HAEGARDA.
- Do not mix HAEGARDA with other medicinal products.
- Visually inspect the final solution for particles and discoloration prior to administration, and whenever solution and container permit. Do not use if particles or discoloration is observed.
- Attach the syringe containing the reconstituted HAEGARDA solution to a hypodermic needle or subcutaneous infusion set and administer by subcutaneous injection. Adapt the rate of administration to the comfort level of the patient.
- Inject in the abdominal area or other subcutaneous injection sites. Rotate injection sites so that the same site is not used repeatedly.
- Administer HAEGARDA at room temperature and within 8 hours after reconstitution. Following administration, discard any unused solution and all administration equipment in an appropriate manner as per local requirements.

3 DOSAGE FORMS AND STRENGTHS

HAEGARDA is available as a white lyophilized powder supplied in single-dose vials containing 2000 or 3000 IU of C1-INH.

- The 2000 IU vial must be reconstituted with 4 mL of Sterile Water for Injection, USP.
- The 3000 IU vial must be reconstituted with 5.6 mL of Sterile Water for Injection, USP.

4 CONTRAINDICATIONS

HAEGARDA is contraindicated in individuals who have experienced life-threatening hypersensitivity reactions, including anaphylaxis, to C1-INH preparations or its excipients [see Description (11)].

5 WARNINGS AND PRECAUTIONS

The physician should discuss the risks and benefits of this product with the patient before prescribing or administering it to the patient [see Patient Counseling Information (17)].

Initiate individualized treatment in case of an acute HAE attack.

5.1 Hypersensitivity

Severe hypersensitivity reactions may occur. The signs and symptoms of hypersensitivity reactions may include hives (local and generalized), tightness of the chest, difficulty breathing, wheezing, hypotension, and/or anaphylaxis during or after injection of HAEGARDA. In case of severe hypersensitivity, discontinue HAEGARDA administration and institute appropriate treatment. Epinephrine should be immediately available for treatment of severe hypersensitivity reaction [see Patient Counseling Information (17)].

5.2 Thromboembolic Events

At the recommended subcutaneous dose, a causal relationship between thromboembolic events (TEEs) and the use of HAEGARDA has not been established [see Patient Counseling Information (17)]. Thrombosis has occurred in treatment attempts with high doses of C1-INH intravenous (I.V.) for prevention or therapy of capillary leak syndrome before, during or after cardiac surgery (unapproved indication and dose).

5.3 Transmissible Infectious Agents

Because HAEGARDA is made from human blood, it may carry a risk of transmitting infectious agents, e.g., viruses, the variant Creutzfeldt-Jakob disease (vCJD) agent and, theoretically, the Creutzfeldt-Jakob disease (CJD) agent. The risk that such products will transmit an infectious agent has been reduced by screening plasma donors for prior exposure to certain viruses, by testing for the presence of certain current virus infections, and by processes demonstrated to inactivate and/or remove certain viruses during manufacturing [see Description (11) and Patient Counseling Information (17)]. Despite these measures, such products may still contain human pathogenic agents, including those not yet known or identified. Thus, the risk of transmission of infectious agents cannot be totally eliminated.

All infections thought by a physician possibly to have been transmitted by HAEGARDA should be reported by lot number, by the physician or other healthcare provider, to the CSL Behring Pharmacovigilance Department at 1-866-915-6958.

6 ADVERSE REACTIONS

Adverse reactions occurring in more than 4% of subjects treated with HAEGARDA were injection site reactions, hypersensitivity, nasopharyngitis and dizziness.

6.1 Clinical Trials Experience

Because clinical studies are conducted under widely varying conditions, adverse reaction rates observed in the clinical trials of a drug cannot be directly compared to rates in the clinical trials of another drug and may not reflect the rates observed in practice.

Of the 90 subjects randomized in the double-blind, placebo-controlled, cross-over study (Study 1) [see Clinical Studies (14)], 86 subjects received at least one dose of HAEGARDA and 86 subjects received at least one dose of placebo (Table 1). A total of 5081 injections of HAEGARDA and placebo were administered over a range of 3 to 19 weeks (median of 16.6 weeks for HAEGARDA; median of 16.3 weeks for placebo). Eligible patients were also able to participate in a randomized, open-label, active treatment-controlled study (Study 2) for up to 140 weeks (n=120).

Table 1. Adverse Reactions in >4% of Subjects Treated with HAEGARDA
MedDRA System Organ Class | Adverse Reaction | HAEGARDA |  |  | Placebo (N=86)
MedDRA System Organ Class | Adverse Reaction | 60 IU/kg (N=43) | 40 IU/kg (N=43) | Overall [Includes subjects who were treated with 40 IU/kg or 60 IU/kg HAEGARDA.] (N=86) | Placebo (N=86)
MedDRA System Organ Class | Adverse Reaction | n (%) | n (%) | n (%) | n (%)
General Disorders and Administration Site Conditions | Injection Site Reaction [Includes: Injection site bruising, coldness, discharge, erythema, hematoma, hemorrhage, induration, edema, pain, pruritus, rash, reaction, scar, swelling, urticaria, warmth.] | 15 (35) | 12 (28) | 27 (31) | 21 (24)
Immune System Disorders | Hypersensitivity [Includes: hypersensitivity, pruritus, rash, and urticaria.] | 3 (7) | 2 (5) | 5 (6) | 1 (1)
Infections and Infestations | Nasopharyngitis | 8 (19) | 1 (2) | 9 (11) | 6 (7)
Nervous System Disorders | Dizziness | 0 (0) | 4 (9) | 4 (5) | 1 (1)
N = number of subjects receiving the treatment; n = number of subjects experiencing ≥1 event.

Of the injection site reactions occurring after treatment with HAEGARDA, 95% were of mild intensity and 83% resolved within 1 day after onset.

Overall, safety data from the open-label study (Study 2), consisting of 59 patients who participated in Study 1 and 61 patients who did not participate in Study 1 (n=120), were consistent with the safety data from the randomized, double-blind, placebo-controlled, crossover, routine prophylaxis trial (Study 1).

7 DRUG INTERACTIONS

No interaction studies have been conducted.

8 USE IN SPECIFIC POPULATIONS

8.1 Pregnancy

Risk Summary

There are no prospective clinical data from HAEGARDA use in pregnant women. C1-INH is a normal component of human plasma. Animal developmental or reproduction toxicity studies have not been conducted with HAEGARDA. In the U.S. general population, the estimated background risk of major birth defects occurs in 2-4% of the general population and miscarriage occurs in 15-20% of clinically recognized pregnancies.

Data

In a retrospective case collection study, 22 pregnant women with type I HAE and ranging in age from 20 to 38 years received C1-INH doses of 500 or 1000 IU per I.V. administration for the treatment of acute attacks before, during, and/or after pregnancy (total of 35 pregnancies). No adverse events were associated with C1-INH treatment before, during, or after pregnancy.^1

In an observational registry (overall 318 subjects) data were collected on 11 pregnancies in 10 subjects (16 to 40 years old) receiving up to 3000 IU C1-INH (I.V. administration) to treat or prevent HAE attacks. No adverse events were associated with C1-INH treatment.^2

In the randomized, open-label, active treatment-controlled, study (Study 2), four pregnant women with type I HAE and ranging in age from 19 to 32 years received C1-INH (S.C. administration). Patients received 40-60 IU/kg per S.C. administration for 4 – 8 weeks (9 - 15 doses) during the first trimester. These women reported no complications during delivery and all women delivered healthy babies.

8.2 Lactation

Risk Summary

There is no information regarding the excretion of HAEGARDA in human milk, the effect on the breastfed infant, or the effects on milk production. The developmental and health benefits of breastfeeding should be considered along with the mother's clinical need for HAEGARDA and any potential adverse effects on the breastfed infant from HAEGARDA or from the underlying maternal condition.

Data

In a retrospective case collection study, breastfeeding was documented for neonates from 21 of 35 births with a median duration of 4.8 months (ranging from 1 to 34 months). Mothers were treated postpartum with C1-INH doses up to 1000 IU per I.V. administration for the treatment of acute HAE attacks. No adverse events to the mothers were associated with C1-INH treatment after pregnancy. No information regarding the effect on the breastfed infant was reported.^1

8.4 Pediatric Use

The safety and effectiveness of HAEGARDA were evaluated in a subgroup of nine patients 8 to <17 years of age, in the randomized, double-blind, placebo-controlled, crossover, routine prophylaxis trial (Study 1) and the randomized, open-label, active treatment-controlled study (Study 2). Results of subgroup analysis by age were consistent with overall study results.

8.5 Geriatric Use

The safety and effectiveness of HAEGARDA were evaluated in a subgroup of nine subjects 65 to 72 years of age, eight subjects who received the high 60 IU/kg dose and one subject who received the 40 IU/kg dose, in the randomized, double-blind, placebo-controlled, crossover, routine prophylaxis trial (Study 1) and in the randomized, open-label, active treatment-controlled study (Study 2). Clinical studies of HAEGARDA did not include sufficient numbers of subjects aged 65 and over to determine whether they respond differently from younger subjects. Other reported clinical experience has not identified differences in responses between the elderly and younger patients. In general, dose selection for an elderly patient should be cautious, usually starting at the low end of the dosing range, reflecting the greater frequency of decreased hepatic, renal, or cardiac function, and of concomitant disease or other drug therapy.

10 OVERDOSAGE

No case of overdose has been reported. Doses corresponding to up to 117 IU/kg S.C. have been administered twice weekly in a fixed-dose clinical study.

11 DESCRIPTION

HAEGARDA is a human plasma-derived, purified, pasteurized, lyophilized concentrate of C1-INH to be reconstituted for S.C. administration. HAEGARDA is prepared from large pools of human plasma from U.S. donors. The potency of C1-INH is expressed in International Units (IU), which is related to the current WHO Standard for C1-INH products.

Reconstituted HAEGARDA has a concentration of 500 IU/mL C1-INH, 65 mg/mL total protein, 10 mg/mL glycine, 8.5 mg/mL sodium chloride and 2.7 mg/mL sodium citrate.

C1 Esterase Inhibitor

C1-INH is a soluble, single-chain highly glycosylated protein containing 478 amino acid residues which belongs to the serine protease inhibitor (serpin) family.

All plasma used in the manufacturing of C1-INH is obtained from U.S. donors and is tested using serological assays for hepatitis B surface antigen and antibodies to HIV-1/2 and HCV. Additionally, the plasma is tested with Nucleic Acid Testing (NAT) for HBV, HCV, HIV-1 and HAV and found to be non-reactive (negative). The plasma is also tested by NAT for Human Parvovirus B19. Only plasma that has passed virus screening is used for production, and the limit for Parvovirus B19 in the fractionation pool is set not to exceed 10^4 IU of Parvovirus B19 DNA per mL.

The manufacturing process for HAEGARDA includes multiple steps that reduce the risk of virus transmission. The virus inactivation/reduction capacity consists of three steps:

- Pasteurization in aqueous solution at 60°C for 10 hours
- Hydrophobic interaction chromatography
- Virus filtration (also called nanofiltration) by two filters, 20 nm and 15 nm, in series.

Viral inactivation and reduction were evaluated in a series of in vitro spiking experiments. The total mean cumulative virus inactivation/reduction is shown in Table 2.

Table 2. Mean Virus Inactivation/Reductions in HAEGARDA
Virus Studied | Pasteurization [log10] | Hydrophobic Interaction Chromatography [log10] | Virus Filtration [log10] | Total Cumulative [log10]
Enveloped Viruses
HIV-1 | ≥6.6 | ≥4.5 | ≥5.1 | ≥16.2
BVDV | ≥9.2 | ≥4.7 | ≥5.3 | ≥19.2
PRV | 6.3 | ≥6.5 | ≥7.1 | ≥19.9
WNV | ≥7.0 | ND | ≥8.0 | ≥15.0
Non-Enveloped Viruses
HAV | ≥6.4 | 2.8 | ≥5.3 | ≥14.5
CPV | 1.4 | 3.9 | 7.1 | 12.4
B19V | 3.9 | ND | ND | NA
HIV-1, Human immunodeficiency virus type 1, a model for HIV-1 and HIV-2
BVDV, Bovine viral diarrhea virus, a model for HCV
PRV, Pseudorabies virus, a model for large enveloped DNA viruses
WNV, West Nile virus
HAV, Hepatitis A virus
CPV, Canine parvovirus
B19V, Human Parvovirus
B19ND, Not determined
NA, Not applicable

12 CLINICAL PHARMACOLOGY

12.1 Mechanism of Action

C1-INH is a normal constituent of human plasma and belongs to the group of serine protease inhibitors (serpins) that includes antithrombin III, alpha1-protease inhibitor, alpha2-antiplasmin, and heparin cofactor II. As with the other inhibitors in this group, C1-INH has an important inhibiting potential on several of the major human cascade systems, including the complement, fibrinolytic and coagulation systems. Regulation of these systems is performed through the formation of complexes between the protease and the inhibitor, resulting in inactivation of both and consumption of the C1-INH.

C1-INH, which is usually activated during the inflammatory process, inactivates its substrate by covalently binding to the reactive site. C1-INH is the only known inhibitor for the C1r and C1s subcomponents of complement component 1 (C1), coagulation factor XIIa, and plasma kallikrein. Additionally, C1-INH is the main inhibitor for coagulation factor XIa of the intrinsic coagulation cascade.

HAE patients have absence or low levels of endogenous or functional C1-INH. Although the events that cause attacks of angioedema in HAE patients are not well defined, it has been postulated that increased vascular permeability and the clinical manifestation of HAE attacks may be primarily mediated through contact system activation. Suppression of contact system activation by C1-INH through the inactivation of plasma kallikrein and factor XIIa is thought to modulate this vascular permeability by preventing the generation of bradykinin. Administration of HAEGARDA replaces the missing or malfunctioning C1-INH protein in patients with HAE.

12.2 Pharmacodynamics

In untreated patients, insufficient levels of functional C1-INH lead to increased activation of C1, which results in decreased levels of complement component 4 (C4). The administration of HAEGARDA increases plasma levels of C1-INH in a dose-dependent manner and subsequently increases plasma concentrations of C4. The C4 plasma concentrations after S.C. administration of 60 IU/kg HAEGARDA were in the normal range (16 to 38 mg/dL).

12.3 Pharmacokinetics

The pharmacokinetics (PK) of C1-INH were described using population PK analysis.

The PK parameters of C1-INH following twice weekly subcutaneous 60 IU/kg dosing are shown in Table 3.

Table 3. Pharmacokinetic Parameter for HAEGARDA (60 IU/kg) from Population Pharmacokinetic Analysis
Parameter | Mean | 95% CI
CL (mL/hr/kg) [Calculated based on median weight of 80.7 kg of the population,] | 1.03 | 0.90-1.17
Vd (L/kg) | 0.05 | 0.04-0.06
Bioavailability % | 42.7 | 35.2-50.2
Cmax % | 60.7 [Geometric mean,] | 31.8-128 [2.5-97.5 percentile of the population,]
Ctrough % | 48.0 | 25.1-102
Tmax (hr) | 59 [Median,] | 23-134
Half-life (hr) [Apparent half-life.] | 69 | 24-251

The steady state PK of S.C. C1-INH is independent of dose between 20-80 IU/kg in HAE subjects.

Studies have not been conducted to evaluate the PK of C1-INH in specific patient populations stratified by gender, race, or the presence of renal or hepatic impairment. Body weight was included as covariate in the population PK analysis of C1-INH in the age range of 8-72 years while age was not a statistically significant covariate. The body weight adjusted clearance is 11% and 10 % higher in children (8 to < 12 years old) and adolescents (12 to < 18 years old) as compared to adult subjects (18 to 72 years), respectively.

13 NONCLINICAL TOXICOLOGY

13.1 Carcinogenesis, Mutagenesis, Impairment of Fertility

No animal studies have been conducted to evaluate the effects of C1-INH on carcinogenesis, mutagenesis, and impairment of fertility.

13.2 Animal Toxicology and/or Pharmacology

Single subcutaneous administration of HAEGARDA in rabbits at dose levels up to approximately 670 IU/kg did not result in adverse findings.

14 CLINICAL STUDIES

The efficacy and safety of HAEGARDA for routine prophylaxis to prevent HAE attacks were demonstrated in a multicenter, randomized, double-blind, placebo-controlled, crossover study (Study 1), and in a multicenter, randomized, open-label, active treatment-controlled study (Study 2).

Study 1:

The study assessed 90 adult and adolescent subjects with symptomatic HAE type I or II. The median (range) age of subjects was 40 (12 to 72) years; 60 subjects were female and 30 subjects were male. Subjects were randomized to receive either 60 IU/kg or 40 IU/kg HAEGARDA in one 16-week treatment period and placebo in the other 16-week treatment period. Patients self-administered HAEGARDA or placebo subcutaneously 2 times per week. Efficacy was evaluated for the last 14 weeks of each treatment period.

Eligible patients were also able to participate in Study 2 for up to 140 weeks. Approximately half of the subjects enrolled in Study 2 also participated in Study 1 (59/120, 49.2%).

Twice per week S.C. doses of 60 IU/kg or 40 IU/kg HAEGARDA resulted in a significant difference in the time-normalized number of HAE attacks (the rate of attacks) relative to placebo (Table 4). The time normalized number of HAE attacks in subjects dosed with 60 IU/kg was 0.52 attacks per month compared to 4.03 attacks per month while receiving placebo (p <0.001). The time normalized number of HAE attacks in subjects dosed with 40 IU/kg was 1.19 attacks per month compared to 3.61 attacks per month while receiving placebo (p <0.001).

Table 4. Time-normalized Number of HAE Attacks (Number/Month)
 | 60 IU/kg HAEGARDA Treatment Sequences (N = 45) |  | 40 IU/kg HAEGARDA Treatment Sequences (N = 45)
 | HAEGARDA | Placebo | HAEGARDA | Placebo
n | 43 | 42 | 43 | 44
Mean (SD) | 0.5 (0.8) | 4.0 (2.3) | 1.2 (2.3) | 3.6 (2.1)
Min, Max | 0.0, 3.1 | 0.6, 11.3 | 0.0, 12.5 | 0.0, 8.9
Median | 0.3 | 3.8 | 0.3 | 3.8
LS Mean (SE) [From a mixed model.] | 0.5 (0.3) | 4.0 (0.3) | 1.2 (0.3) | 3.6 (0.3)
95% CI for LS Mean | (0.0, 1.0) | (3.5, 4.6) | (0.5, 1.9) | (3, 4.3)
Treatment difference (within-subjects) | 60 IU/kg HAEGARDA – Placebo |  | 40 IU/kg HAEGARDA – Placebo
LS Mean (95% CI) | -3.5 (-4.2, -2.8) |  | -2.4 (-3.4, -1.5)
p-value | < 0.001 |  | < 0.001
CI = confidence interval; HAE = hereditary angioedema; N = number of randomized subjects;
n = number of subjects with data; LS = Least squares.

The median (25th, 75th percentile) percentage reduction in the time-normalized number of HAE attacks relative to placebo was 95% (79, 100) on 60 IU/kg HAEGARDA and 89% (70, 100) on 40 IU/kg HAEGARDA among subjects with evaluable data in both treatment periods.

The percentage of responders (95% CI) with a ≥50% reduction in the time‑normalized number of HAE attacks on HAEGARDA relative to placebo was 83% (73%, 90%). Ninety percent (90%) of subjects on 60 IU/kg responded to treatment and 76% of subjects on 40 IU/kg responded to treatment.

The percentages of subjects (95% CI) with ≥70% and ≥90% reductions in the time‑normalized number of HAE attacks on HAEGARDA relative to placebo were 74% (64%, 83%) and 50% (39%, 61%), respectively. The percentages of subjects with ≥70% and ≥90% reductions in comparison to placebo in the time-normalized number of HAE attacks were 83% and 58% on 60 IU/kg and 67% and 43% on 40 IU/kg. Seventy-one percent (71%) of subjects on 60 IU/kg and 53% of subjects on 40 IU/kg had ≥1 HAE attack per 4 week period on placebo and <1 HAE attack per 4 week period on HAEGARDA.

A total of 40% of subjects on 60 IU/kg and 38% of subjects on 40 IU/kg were attack-free, and the median rate of HAE attacks per month was 0.3 on both doses.

HAEGARDA resulted in a significant difference in the time-normalized number of uses of rescue medication (the rate of rescue medication use) relative to placebo. A dose of 60 IU/kg resulted in a mean rate of rescue medication of 0.3 uses per month, compared to 3.9 uses per month with placebo. A dose of 40 IU/kg resulted in a mean rate of rescue medication use of 1.1 uses per month, compared to 5.6 uses per month with placebo.

Study 2:

The study assessed 120 adult and pediatric subjects with symptomatic HAE type I or II. The median (range) age of subjects was 41.0 (8-72) years. Patients with a monthly attack rate of 4.3 in 3 months before entry in the study were enrolled and treated for a mean of 1.4 years; 41 patients (34.2%) had more than 2 years of exposure. Mean steady-state C1-INH functional activity increased to 52.0% with 40 IU/kg and 66.6% with 60 IU/kg. Incidence of adverse events was similar in both dose groups (12.0 and 8.6 events per patient-year for 40 IU/kg and 60 IU/kg, respectively). The percentages of subjects with ≥50% reductions in the time-normalized number of HAE attacks on HAEGARDA relative to the time-normalized number of HAE attacks at baseline were 93.1% and 93.1% in 40 IU/kg and 60 IU/kg treatment arms, respectively. The percentages of subjects with time normalized HAE attack frequency of < 1 HAE attack per 4-week period were 79.7% on 40 IU/kg and 86.9% on 60 IU/kg. For 40 IU/kg and 60 IU/kg, median annualized attack rates were 1.0 and 1.0, respectively, and median rescue medication use was 0.0 and 0.0 times per year, respectively. The proportion of HAE attack-free subjects throughout the study duration with a maximum exposure of >2.5 years was 35.6% and 44.3% in the 40 IU/kg and 60 IU/kg treatment arms, respectively.

15 REFERENCES

1. Martinez-Saguer I, Rusicke E, Aygören-Pürsün E, et al. Characterization of acute hereditary angioedema attacks during pregnancy and breast-feeding and their treatment with C1 inhibitor concentrate. Am J Obstet Gynecol. 2010;203:131.e1-7.
2. Fox J, Vegh AB, Martinez-Saguer I, et al. Safety of a C1-inhibitor concentrate in pregnant women with hereditary angioedema. Allergy Asthma Proc. 2017;38(3):216-221

16 HOW SUPPLIED/STORAGE AND HANDLING

HAEGARDA is supplied in a kit containing a lyophilized powder in a single-dose vial.

HAEGARDA is packaged with Sterile Water for Injection, USP (4 mL for reconstitution of 2000 IU or 5.6 mL for reconstitution of 3000 IU) and one Mix2Vial filter transfer set. Not made with natural rubber latex.

Table 5. How Supplied
Nominal Strength | Fill Size Color Indicator | Kit NDC
2000 IU | Fuschia | 63833-828-02
3000 IU | Yellow | 63833-829-02

Storage and Handling

- When stored at temperatures up to 30°C (86°F), HAEGARDA is stable for the period indicated by the expiration date on the carton and vial label.
- Keep HAEGARDA in its original carton until ready to use.
- Do not freeze.
- Protect from light.
- Discard any unused product and all used disposable supplies.

17 PATIENT COUNSELING INFORMATION

See FDA-approved patient labeling (Patient Product Information).

All risks and benefits of HAEGARDA should be discussed with the patient/caregiver before prescribing or administering it to the patient.

Inform patients/caregivers to immediately report the following to their physician:

- Signs and symptoms of allergic hypersensitivity reactions, such as hives, tightness of the chest, difficulty breathing, wheezing, hypotension and/or anaphylaxis experienced during or after injection of HAEGARDA [see Warnings and Precautions (5.1)].
- Signs and symptoms of a thromboembolic event, including pain and/or swelling of an arm or leg with warmth over the affected area, discoloration of an arm or leg, unexplained shortness of breath, chest pain or discomfort that worsens on deep breathing, unexplained rapid pulse, numbness or weakness on one side of the body [see Warnings and Precautions (5.2)].

Inform all patients/caregivers:

- HAEGARDA is indicated for HAE prophylaxis and should not be used for the treatment of acute HAE attacks. Patients/caregivers should be counselled regarding the appropriate course of action if breakthrough HAE attacks occur while on HAEGARDA, including:
  - Individualized rescue treatment for acute HAE attacks.
  - Situations in which to seek immediate medical attention, such as acute laryngeal HAE attacks.
- Patients/caregivers must ensure an adequate supply of HAEGARDA when traveling.
- Because HAEGARDA is made from human blood, it may carry a risk of transmitting infectious agents, e.g., viruses, the variant Creutzfeldt-Jakob disease (vCJD) agent and, theoretically, the Creutzfeldt-Jakob disease (CJD) agent [see Warnings and Precautions (5.3) and Description (11)].
- Patients with known risk factors for thromboembolic events are at an increased risk for these events [see Warnings and Precautions (5.2)].
- Ensure that the patient/caregiver has access to and has received training in the administration of subcutaneous epinephrine and/or other appropriate supportive therapy for the treatment of any acute anaphylactic or severe hypersensitivity reaction [see Warnings and Precautions (5.1)].

Advise female patients:

- Patients should notify their physician if they become pregnant or intend to become pregnant while taking HAEGARDA [see Use in Specific Populations (8.1)].
- Patients should notify their physician if they are breastfeeding or plan to breastfeed while taking HAEGARDA [see Use in Specific Populations (8.2)].

Self-administration - Ensure that the patient/caregiver receives clear instructions and training on S.C. administration in the home or other appropriate setting and has demonstrated the ability to perform S.C. injection.

- Ensure the patient (or caregiver) has the necessary dexterity and comprehension to be trained to self-administer.
- Instruct patients/caregivers to record the lot number from the HAEGARDA vial label every time they use HAEGARDA.

The attached HAEGARDA "Patient Product Information (PPI)" contains more detailed instructions for patients/caregivers who will be self-administering HAEGARDA.

Manufactured by:
CSL Behring GmbH
35041 Marburg, Germany
US License No. 1765

Distributed by:
CSL Behring LLC
Kankakee, IL 60901 USA

Mix2Vial® is a registered trademark of West Pharma. Services IL, Ltd., a subsidiary of West Pharmaceuticals Services, Inc.

FDA-Approved Patient Labeling – Patient Product Information (PPI)

HAEGARDA (hay-GAR-duh)
C1 Esterase Inhibitor Subcutaneous (Human)
Freeze-Dried Powder for Reconstitution

This leaflet summarizes important information about HAEGARDA. Please read it carefully before using HAEGARDA and each time you get a refill. There may be new information provided. This information does not take the place of talking with your healthcare provider, and it does not include all of the important information about HAEGARDA. If you have any questions after reading this, ask your healthcare provider.

Do not attempt to self-administer unless you have been taught how by your healthcare provider.

What is HAEGARDA?

HAEGARDA is an injectable medicine used to prevent swelling and/or painful attacks in patients 6 years of age and older with Hereditary Angioedema (HAE). HAE is caused by the poor functioning or lack of a protein called C1 that is present in your blood and helps control inflammation (swelling) and parts of the immune system. HAEGARDA contains C1 esterase inhibitor (C1-INH), a protein that helps control C1.

HAEGARDA should not be used to treat an acute HAE attack. In case of an acute HAE attack, initiate individualized treatment as discussed with your prescribing health care professional.

Who should not use HAEGARDA?

You should not use HAEGARDA if you have experienced life-threatening immediate hypersensitivity reactions, including anaphylaxis, to the product.

What should I tell my healthcare provider before using HAEGARDA?

Tell your healthcare provider about all of your medical conditions, including if you:

- Are pregnant or planning to become pregnant. It is not known if HAEGARDA can harm your unborn baby.
- Are breastfeeding or plan to breastfeed. It is not known if HAEGARDA passes into your milk and if it can harm your baby.
- Have a history of blood clotting problems. Blood clots have occurred in patients receiving HAEGARDA. Very high doses of C1-INH could increase the risk of blood clots. Tell your healthcare provider if you have a history of heart or blood vessel disease, stroke, blood clots, or have thick blood, an indwelling catheter/access device in one of your veins, or have been immobile for some time. These things may increase your risk of having a blood clot after using HAEGARDA. Also, tell your healthcare provider what drugs you are using, as some drugs, such as birth control pills or certain androgens, may increase your risk of developing a blood clot.

Tell your healthcare provider and pharmacist about all of the medicines you take, including all prescription and non-prescription medicines such as over-the-counter medicines, supplements, or herbal remedies.

What are the possible side effects of HAEGARDA?

Allergic reactions may occur with HAEGARDA. Call your healthcare provider or seek emergency support services right away if you have any of the following symptoms after using HAEGARDA:

- wheezing
- difficulty breathing
- chest tightness
- turning blue (look at lips and gums)
- fast heartbeat
- swelling of the face
- rash or hives

Signs of a blood clot include:

- pain and/or swelling of an arm or leg with warmth over the affected area
- discoloration of an arm or leg
- unexplained shortness of breath
- chest pain or discomfort that worsens on deep breathing
- unexplained rapid pulse
- numbness or weakness on one side of the body

Because HAEGARDA is made from human blood, it may carry a risk of transmitting infectious agents, e.g., viruses, the variant Creutzfeldt-Jakob disease (vCJD) agent and, theoretically, the Creutzfeldt-Jakob disease (CJD) agent.

The most common side effects with HAEGARDA are injection site reactions (pain, redness, swelling), hypersensitivity (itching and rash), nasopharyngitis (runny or stuffy nose, sneezing, watery eyes) and dizziness.

These are not all the possible side effects of HAEGARDA.

Tell your healthcare provider about any side effect that bothers you or that does not go away. You can also report side effects to the FDA at 1-800-FDA-1088.

How should I store HAEGARDA?

- Keep the non-reconstituted HAEGARDA in its original carton to protect from light until ready to use.
- When stored at temperatures up to 30°C (86°F), HAEGARDA is stable for the period indicated by the expiration date on the carton and vial label.
- Do not freeze.

What else should I know about HAEGARDA?

Medicines are sometimes prescribed for purposes other than those listed here. Do not use HAEGARDA for a condition for which it is not prescribed. Do not share HAEGARDA with other people, even if they have the same symptoms that you have.

This leaflet summarizes the most important information about HAEGARDA. If you would like more information, talk to your healthcare provider. You can ask your healthcare provider or pharmacist for information about HAEGARDA that was written for healthcare professionals. For more information, go to www.HAEGARDA.com or call 1-877-236-4423.

What should I know about self-administration?

- You should prepare the prescribed dose of HAEGARDA for self-administration as directed by your healthcare provider.

Instructions for Use

- Do not attempt to self-administer unless you have been taught how by your healthcare provider.
- See the step-by-step instructions for injecting HAEGARDA at the end of this leaflet. You should always follow the specific instructions given by your healthcare provider. The steps listed below are general guidelines for using HAEGARDA. If you are unsure of the steps, please contact your healthcare provider or pharmacist before using.
- Your healthcare provider will prescribe the dose that you should administer, which is based on your body weight.
- Call your healthcare provider if you miss a dose of HAEGARDA.
- Talk to your healthcare provider before traveling to make sure you have an adequate supply of HAEGARDA.
- Use a new needle for each HAEGARDA injection. Do not reuse or share your needles with other people. You may give other people a serious infection, or get a serious infection from them.

Reconstitution and Administration

- The 2000 IU HAEGARDA vial contains C1-INH as a lyophilized concentrate for reconstitution with 4 mL of Sterile Water for Injection, USP provided; or, the 3000 IU HAEGARDA vial contains C1-INH as a lyophilized concentrate for reconstitution with 5.6 mL of Sterile Water for Injection, USP provided.
- Check the expiration date on the product vial label. Do not use beyond the expiration date.
- Work on a clean surface and wash hands before performing the following procedures.
- Use either the Mix2Vial transfer set provided with HAEGARDA or a commercially available double-ended needle and vented filter spike.
- Prepare and administer using aseptic techniques.
- Each vial of HAEGARDA is for single-dose only. Promptly use the reconstituted solution. The solution must be used within 8 hours. Discard partially used vials. HAEGARDA contains no preservative.
- After reconstitution and prior to administration inspect HAEGARDA. The reconstituted solution should be colorless, clear, and free from visible particles. Do not use if the solution is cloudy, discolored, or contains particulates.

Reconstitution

The procedures below are provided as general guidelines for the reconstitution of HAEGARDA.

HAEGARDA Reconstitution Instructions

1. Ensure that the HAEGARDA vial and Sterile Water for Injection (diluent) vial are at room temperature.

2. Place the HAEGARDA vial, diluent vial and Mix2Vial transfer set on a flat surface.

3. Remove flip caps from the HAEGARDA and diluent vials.

4. Wipe the stoppers with an alcohol swab and allow to dry prior to opening the Mix2Vial transfer set package.

5. Open the Mix2Vial transfer set package by peeling away the lid (Figure 1). Do not remove the device from the package.

Figure 1

6. Place the diluent vial on a flat surface and hold the vial tightly. Grip the Mix2Vial transfer set together with the clear package and push the plastic spike at the blue end of the Mix2Vial transfer set firmly through the center of the stopper of the diluent vial (Figure 2).

Figure 2

7. Carefully remove the clear package from the Mix2Vial transfer set. Do not remove the Mix2Vial transfer set or touch the exposed end of the device (Figure 3).

Figure 3

8. With the HAEGARDA vial placed firmly on a flat surface, invert the diluent vial with the Mix2Vial transfer set attached and push the plastic spike of the transparent adapter firmly through the center of the stopper of the HAEGARDA vial (Figure 4). The diluent will automatically transfer into the HAEGARDA vial.

Figure 4

9. With the diluent and HAEGARDA vial still attached to the Mix2Vial transfer set, gently swirl the HAEGARDA vial to ensure that the powder is fully dissolved (Figure 5). Do not shake the vial.

Figure 5

10. With one hand, grasp the HAEGARDA side of the Mix2Vial transfer set and with the other hand grasp the blue diluent side of the Mix2Vial transfer set, and unscrew the set into two pieces (Figure 6).

Figure 6

11. Draw air into an empty, sterile syringe. Use a silicone-free syringe. While the HAEGARDA vial is upright, screw the syringe to the Mix2Vial transfer set. Inject air into the HAEGARDA vial.

12. While keeping the syringe plunger pressed, invert the system upside down and draw the concentrate into the syringe by pulling the plunger back slowly (Figure 7).

Figure 7

13. Disconnect the filled syringe by unscrewing it from the Mix2Vial transfer set (Figure 8). The reconstituted solution should be colorless, clear, and free from visible particles. Do not use if particles or discoloration are observed.

Figure 8

14. Use immediately or within 8 hours of reconstitution. Store reconstituted solution at room temperature. Do not refrigerate.

15. If the dose requires more than one vial, use a separate, unused Mix2Vial transfer set and diluent vial for each product vial. Repeat steps 10-12 to pool the contents of the vials into one syringe.

Self (or caregiver)-Administration (subcutaneous administration)

Your healthcare provider will teach you (or caregiver) how to safely administer HAEGARDA. Once you (or caregiver) learn how to administer, follow the instructions provided below.

HAEGARDA administration instructions apply to patients, 6 years of age and older.

HAEGARDA Self (or caregiver)-Administration Instructions

Step 1: Assemble supplies

Gather the HAEGARDA syringe, the following disposable supplies (not provided with HAEGARDA), and other items (sharps or other container, treatment diary or log book):

- Hypodermic needle or S.C. infusion set
- Sterile syringe (Use a silicone-free syringe)
- Alcohol wipes
- Gloves (if recommended by the healthcare provider)

Step 2: Clean surface

- Thoroughly clean a table or other flat surface using alcohol wipes.

Step 3: Wash hands

- Thoroughly wash and dry your hands.
- If you have been told to wear gloves when preparing the infusion, put the gloves on.

Step 4: Prepare injection site

- Select an area on the abdomen (stomach) or another site for the injection as discussed with your doctor (Figure 9).

Figure 9

- Use a different place from the last injection; you should rotate the places where you are injecting.
- New injection sites should be at least 2 inches (5 centimeters) away from the place where you gave yourself an injection before.
- Never give an injection in areas where the skin is itchy, swollen, painful, bruised, or red.
- Avoid giving injections in places where you have scars or stretch marks.
- Clean the skin at the injection site with an alcohol swab and let the skin dry (Figure 10).

Figure 10

Step 5: Injection in the abdominal area

As instructed by the healthcare provider:

- Attach a hypodermic needle or S.C. infusion set (butterfly) as instructed by the healthcare provider. Prime the needle or tubing as required and instructed.

Injection with Hypodermic Needle:

- Insert the needle into the fold of skin (Figure 11).

Figure 11

Injection by S.C Infusion Set:

- Insert the needle into the fold of skin (Figure 12).

Figure 12

Step 6: Clean up

- After injecting the entire amount of HAEGARDA, remove the needle.
- Discard any unused solution and all administration equipment in an appropriate manner as per local requirements.

Step 7: Record treatment

Record the lot number from the HAEGARDA vial label in the treatment diary or log book with the date and time of infusion every time you use HAEGARDA.

Resources at CSL Behring available to the patient:
For Adverse Reaction Reporting contact:
CSL Behring Pharmacovigilance Department at 1-866-915-6958

Contact CSL Behring to receive more product information:
Customer Support 1-800-683-1288

For more information, visit www.HAEGARDA.com.

Manufactured by:
CSL Behring GmbH
35041 Marburg, Germany
US License No. 1765

Distributed by:
CSL Behring LLC
Kankakee, IL 60901 USA

Mix2Vial® is a registered trademark of West Pharma. Services IL, Ltd., a subsidiary of West Pharmaceuticals Services, Inc.

PRINCIPAL DISPLAY PANEL - Kit Carton - 2000 IU

NDC 63833-828-02
One single-dose vial and Sterile Water for Injection, USP
2000 IU

C1 Esterase Inhibitor
Subcutaneous (Human)
HAEGARDA®

For Subcutaneous Administration Only
Rx only

CSL Behring

PRINCIPAL DISPLAY PANEL - Kit Carton - 3000 IU

NDC 63833-829-02
One single-dose vial and Sterile Water for Injection, USP
3000 IU

C1 Esterase Inhibitor
Subcutaneous (Human)
HAEGARDA®

For Subcutaneous Administration Only
Rx only

CSL Behring